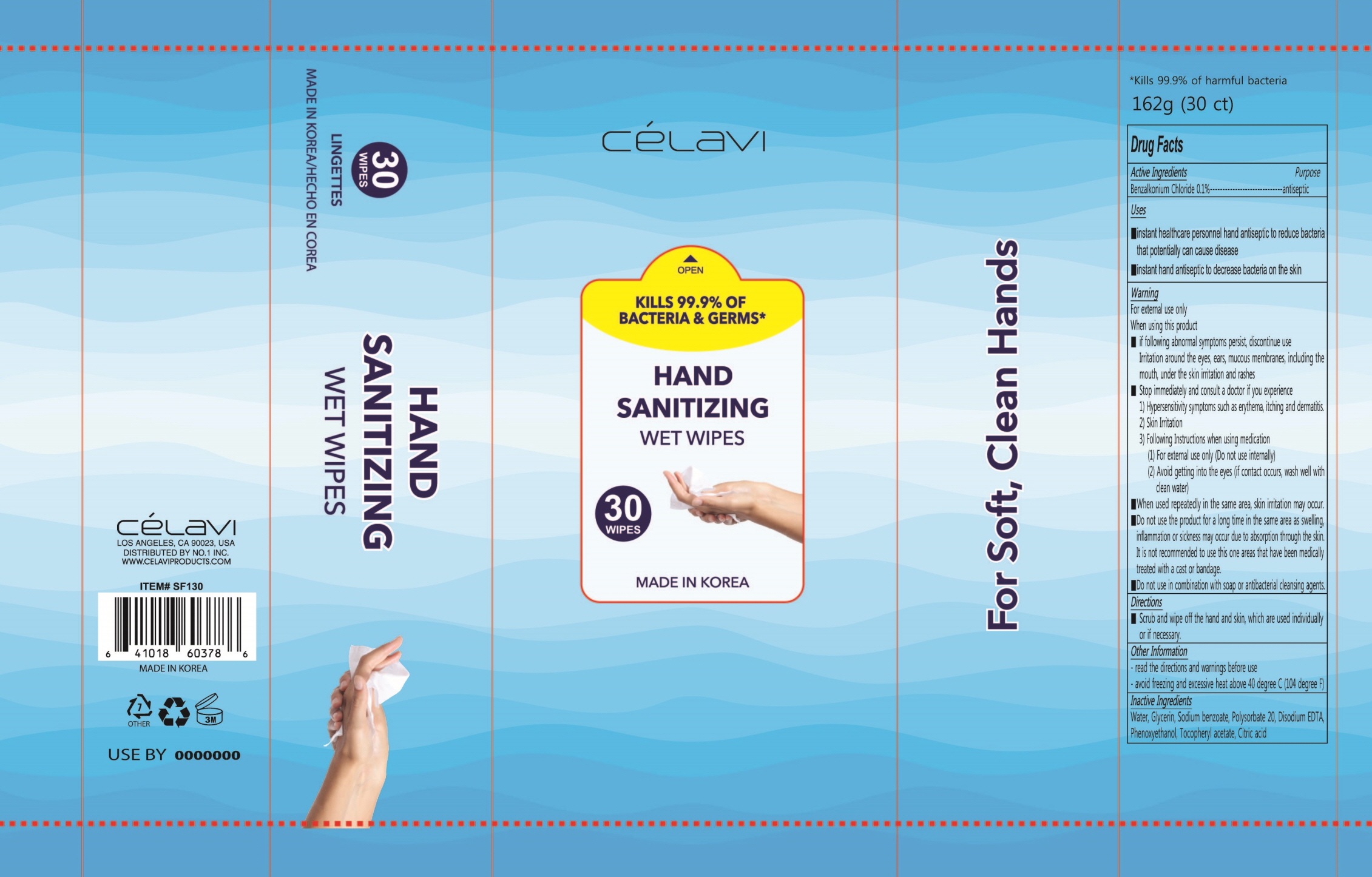 DRUG LABEL: CELAVI HAND SANITIZING WET WIPES
NDC: 75770-010 | Form: LIQUID
Manufacturer: BLANC MER
Category: otc | Type: HUMAN OTC DRUG LABEL
Date: 20201210

ACTIVE INGREDIENTS: BENZALKONIUM CHLORIDE 0.16 g/162 g
INACTIVE INGREDIENTS: WATER; GLYCERIN; SODIUM BENZOATE; Polysorbate 20; EDETATE DISODIUM ANHYDROUS; PHENOXYETHANOL; .ALPHA.-TOCOPHEROL ACETATE; CITRIC ACID MONOHYDRATE

Drug Facts

ACTIVE INGREDIENT

Benzalkonium Chloride 0.1%

INACTIVE INGREDIENTS

Water, Glycerin, Sodium benzoate, Polysorbate 20, Disodium EDTA, Phenoxyethanol, Tocopheryl acetate, Citric acid

PURPOSE

antiseptic

KEEP OUT OF REACH OF CHILDREN

Uses

■instant healthcare personnel hand antiseptic to reduce bacteria that potentially can cause disease

■instant hand antiseptic to decrease bacteria on the skin

WARNINGS

For external use only

When using this product
■ if following abnormal symptoms persist, discontinue use
Irritation around the eyes, ears, mucous membranes, including the mouth, under the skin irritation and rashes
■ Stop immediately and consult a doctor if you experience
1) Hypersensitivity symptoms such as erythema, itching and dermatitis.
2) Skin Irritation
3) Following Instructions when using medication
(1) For external use only (Do not use internally)
(2) Avoid getting into the eyes (if contact occurs, wash well with clean water)
■ When used repeatedly in the same area, skin irritation may occur.
■Do not use the product for a long time in the same area as swelling, inflammation or sickness may occur due to absorption through the skin.
It is not recommended to use this one areas that have been medically treated with a cast or bandage.
■Do not use in combination with soap or antibacterial cleansing agents.

Directions

■ Scrub and wipe off the hand and skin, which are used individually or if necessary.

Other information

■ Read the directions and warnings before use

■ Avoid freezing and excessive heat above 40 ℃ (104 ℉)